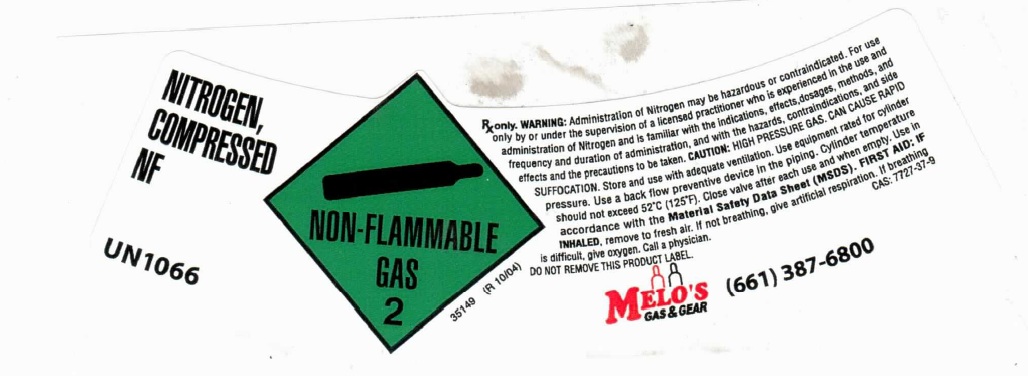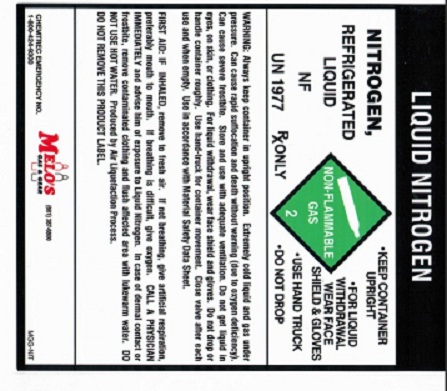 DRUG LABEL: Nitrogen
NDC: 24533-002 | Form: GAS
Manufacturer: Melo's Gas and Gear, Inc.
Category: prescription | Type: HUMAN PRESCRIPTION DRUG LABEL
Date: 20120626

ACTIVE INGREDIENTS: Nitrogen 990 mL/1 L

Nitrogen

PACKAGE LABEL

NITROGEN, COMPRESSED NF
UN1066
NON-FLAMMABLE GAS 2
Rx
only. WARNING: Administration of Nitrogen may be hazardous or
contraindicated. For use only by or under the supervision of a licensed
practitioner who is experienced in the use and administration of
Nitrogen and is familiar with the indications, effects, dosages,
methods, and frequency and duration of administration, and with the
hazards, contraindications, and side effects and the precautions to be
taken. CAUTION: HIGH PRESSURE GAS. CAN CAUSE RAPID SUFFOCATION. Store
and use with adequate ventilation. Use equipment rated for cylinder
pressure. Use a back flow preventive device in the piping. Cylinder
temperature should not exceed 52 degrees C (125 degrees F). Close valve
after each use and when empty. Use in accordance with the Material
Safety Data Sheet (MSDS). FIRST AID: IF INHALED, remove to fresh air.
If not breathing, give artificial respiration. If breathing is
difficult, give oxygen. Call a physician. CAS: 7727-37-9
DO NOT REMOVE THIS PRODUCT LABEL
MELO'S GAS AND GEAR
(661) 387-6800

PACKAGE LABEL

LIQUID NITROGEN
NITROGEN, REFRIGERATED LIQUID NF UN 1977
RX ONLY
NON-FLAMMABLE GAS 2
KEEP CONTAINER UPRIGHT. FOR LIQUID WITHDRAWAL WEAR FACE SHIELD AND GLOVES. USE HAND TRUCK. DO NOT DROP.
WARNING: Always keep container in upright position. Extremely cold liquid and gas under pressure. Can cause rapid suffocation and death without warning (due to oxygen deficiency). Can cause severe frostbite. Store and use with adequate ventilation. Do not get liquid in eyes, on skin, or clothing. For liquid withdrawal, wear face shield and gloves. Do not drop or handle container roughly. Use hand-truck for container movement. Close valve after each use and when empty. Use in accordance with Material Safety Data Sheet.
FIRST AID: IF INHALED, remove to fresh air. If not breathing, give artificial respiration, preferably mouth to mouth. If breathing is difficult, give oxygen. CALL A PHYSICIAL IMMEDIATELY and advise him of exposure to Liquid Nitrogen. In case of dermal contact or frostbite, remove contaminated clothing and flush affected area with lukewarm water. DO NOT USE HOT WATER. Producted by Air Liquefaction Process.DO NOT REMOVE THIS PRODUCT LABEL.
CHEMTREC EMERGENCY NO. 1-800-424-9300
MELO'S GAS AND GEAR (661) 387-6800